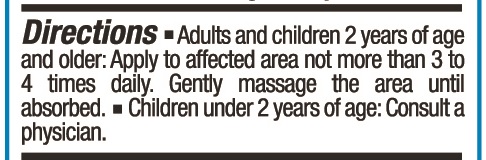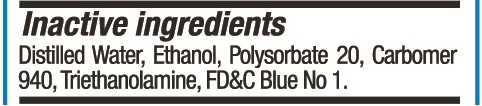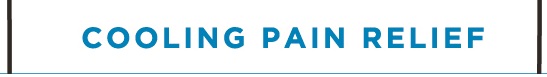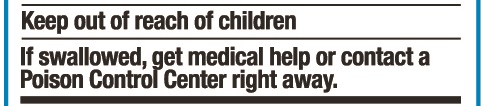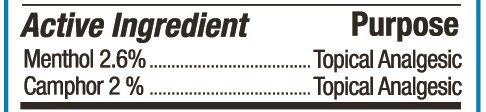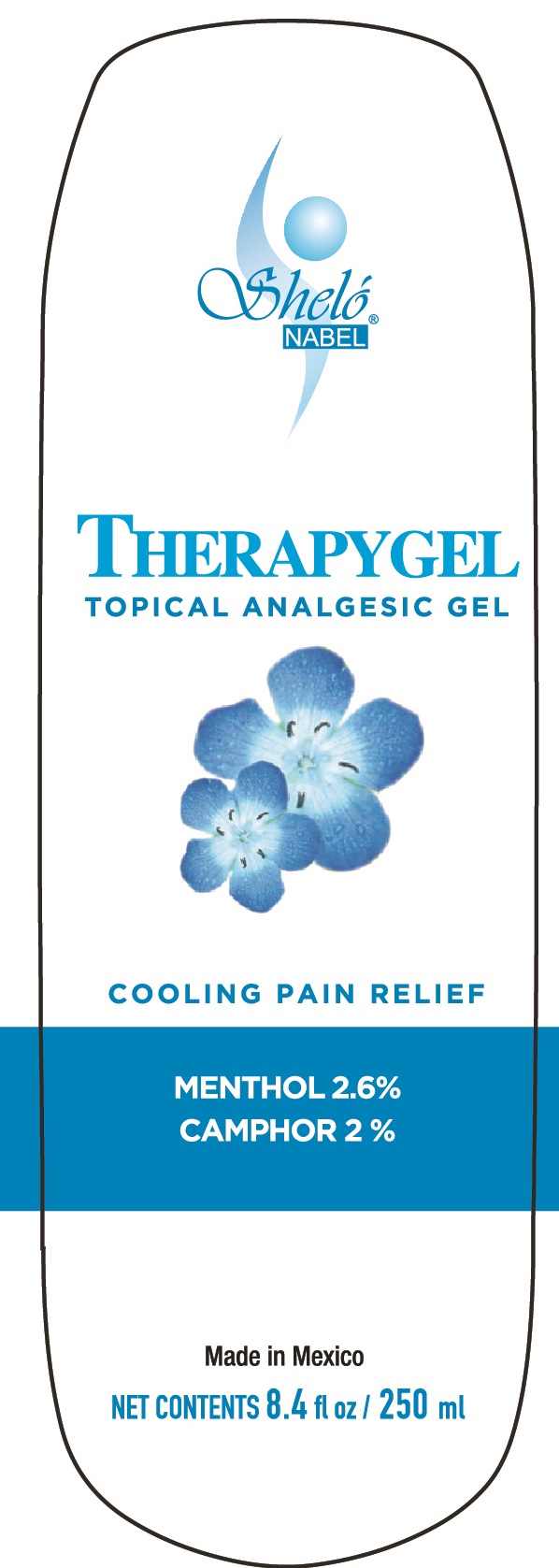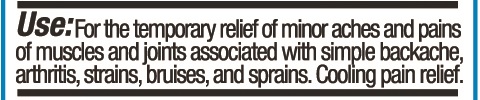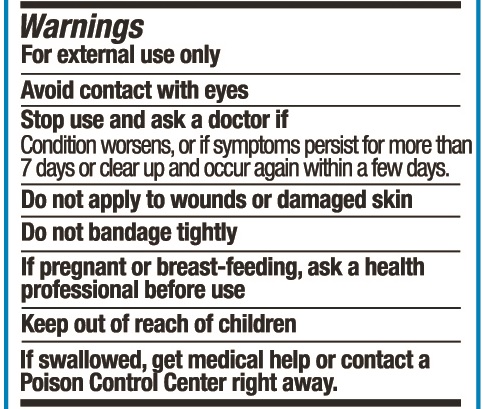 DRUG LABEL: Shelo NABEL TherapyGel
NDC: 71424-1061 | Form: GEL
Manufacturer: Corporativo Serysi S de R L de C V
Category: otc | Type: HUMAN OTC DRUG LABEL
Date: 20191015

ACTIVE INGREDIENTS: MENTHOL, UNSPECIFIED FORM 26 mg/1 g; CAMPHOR (SYNTHETIC) 20 mg/1 g
INACTIVE INGREDIENTS: POLYSORBATE 20

Sheló NABEL Therapygel Topical Analgesic Gel